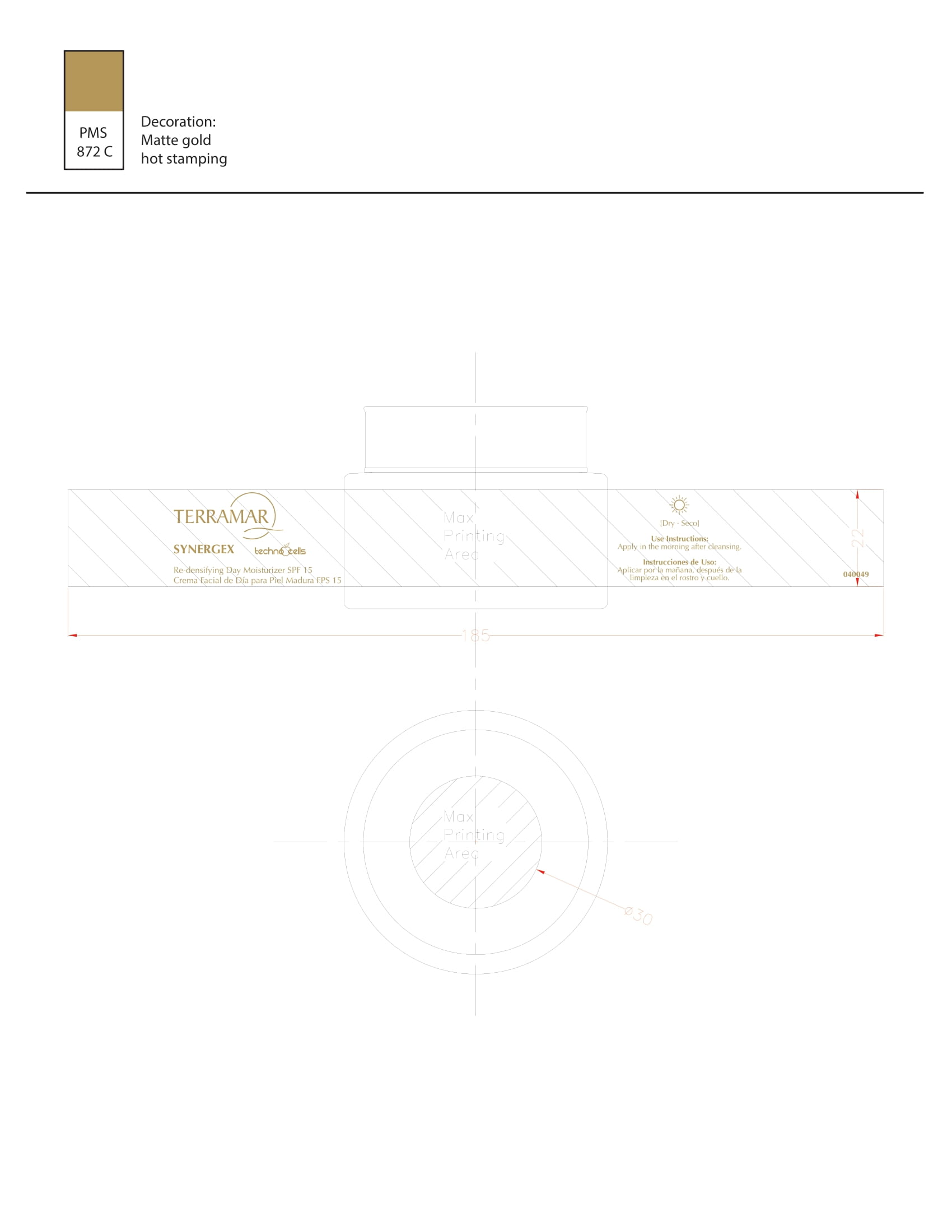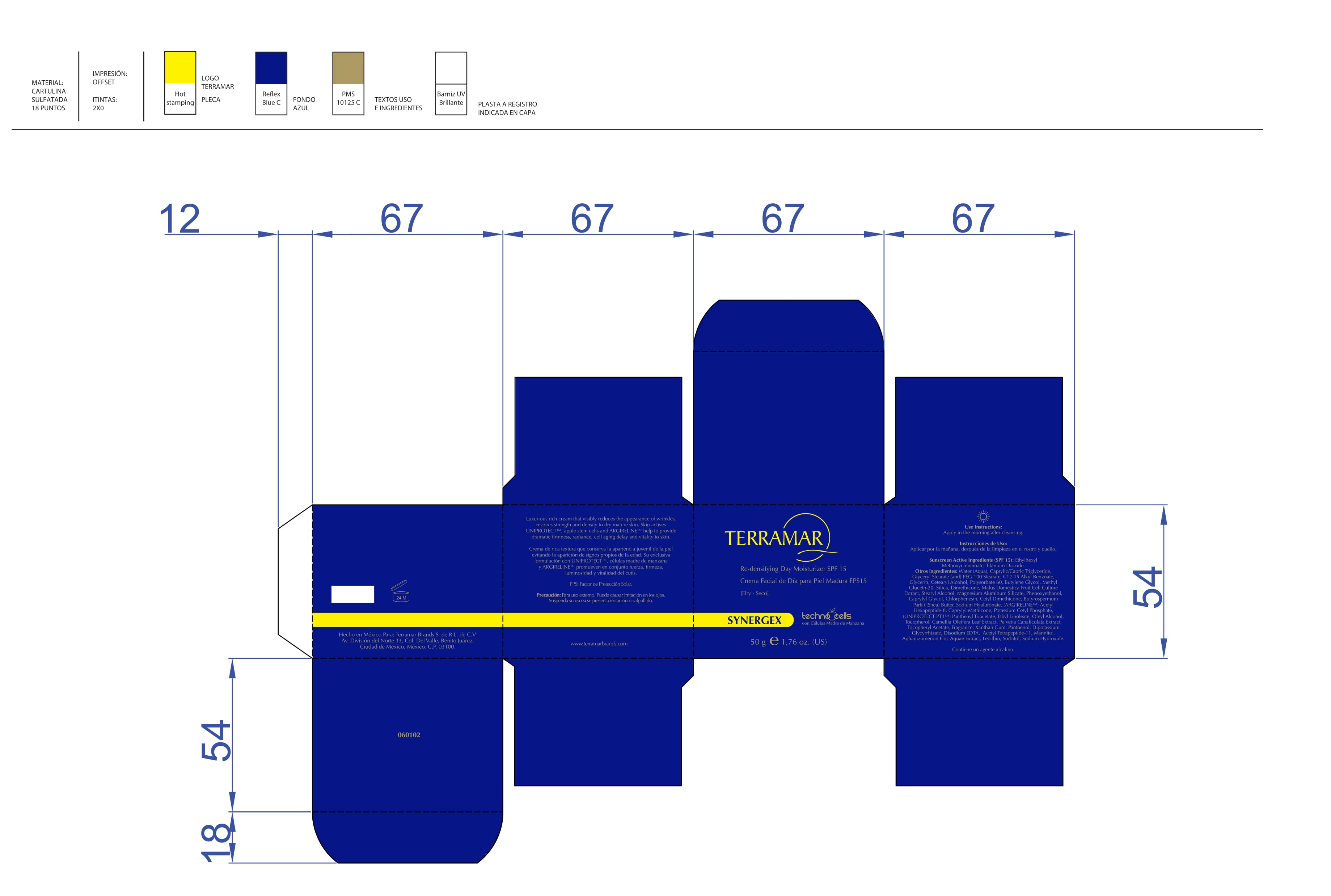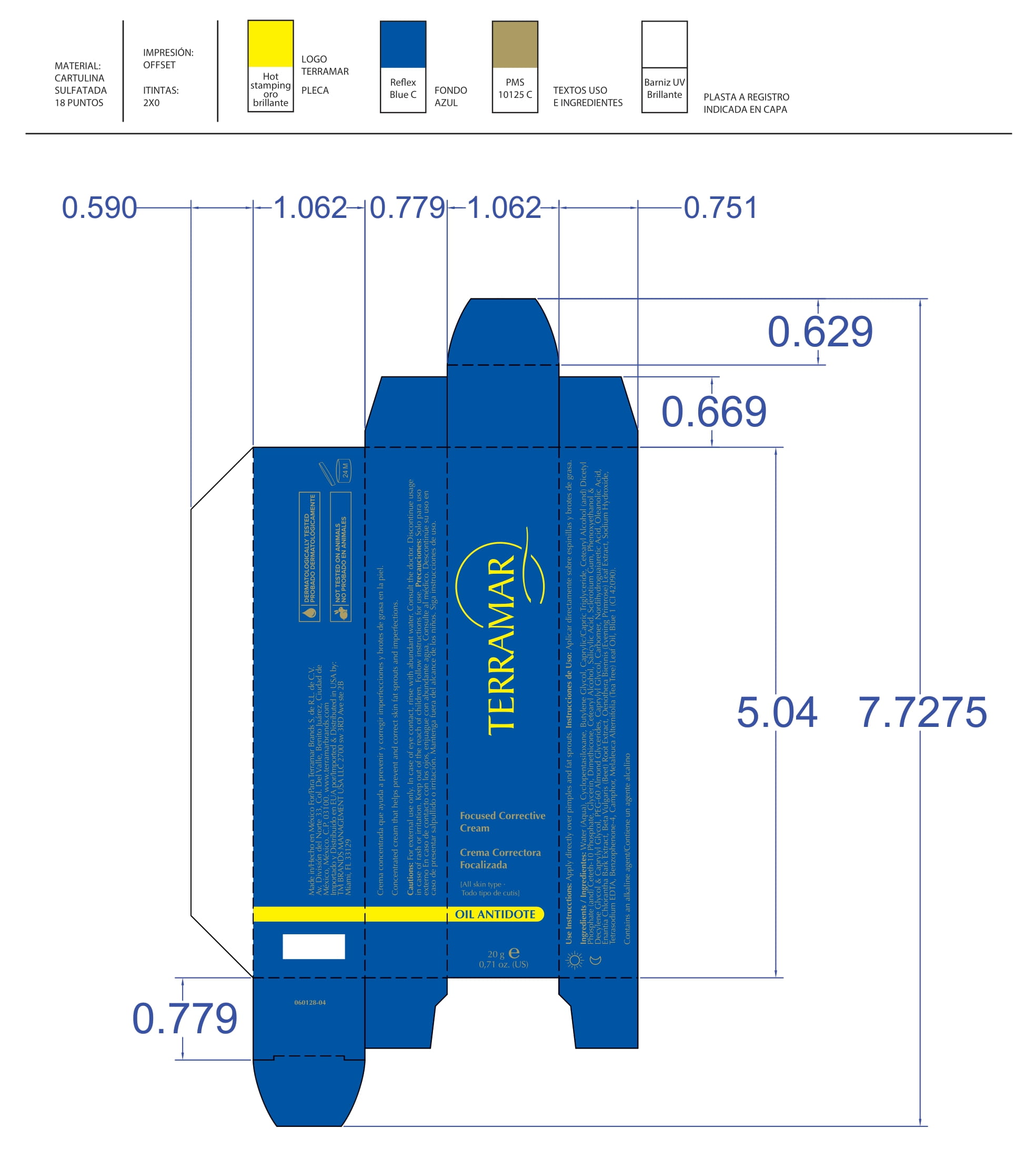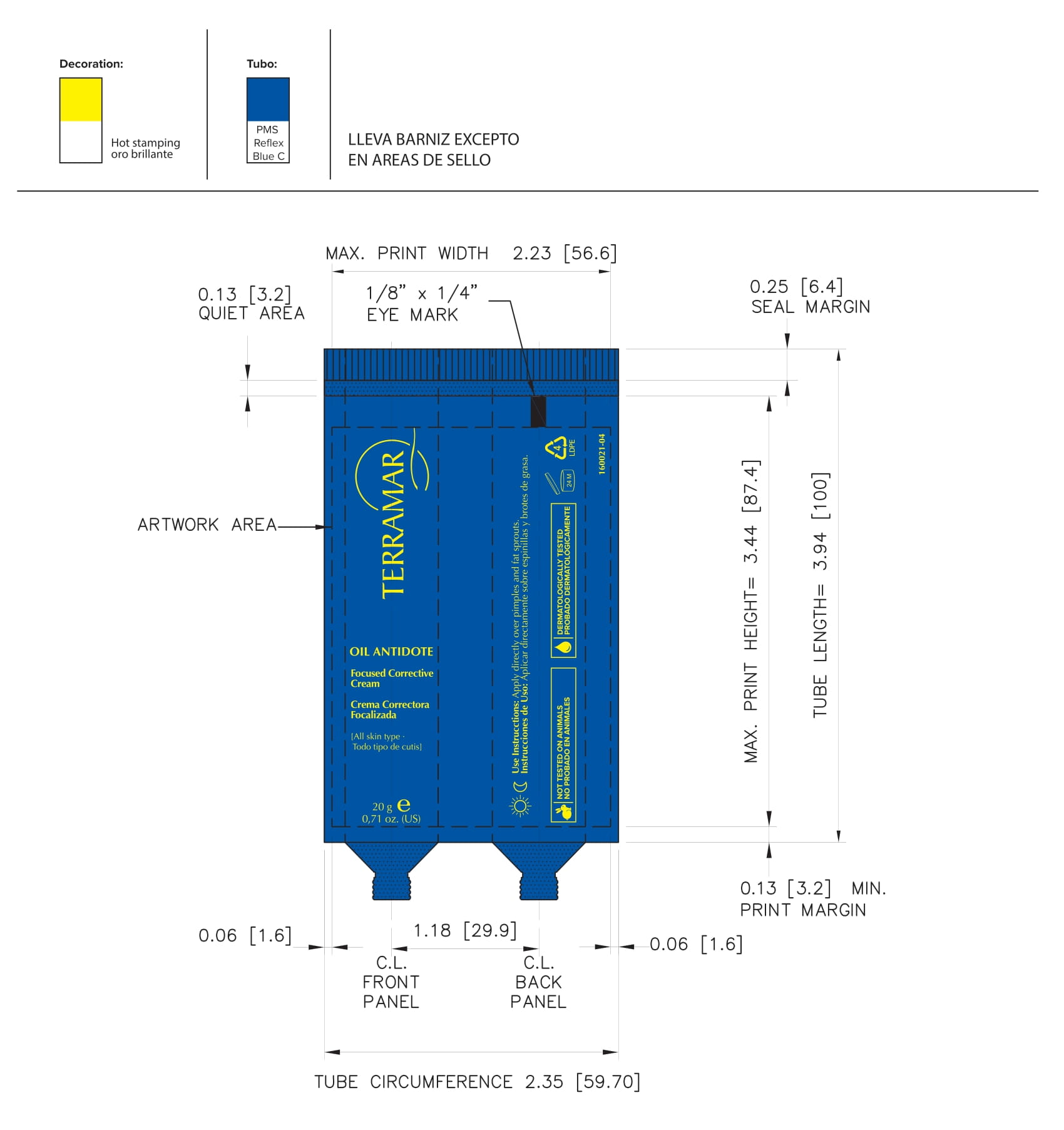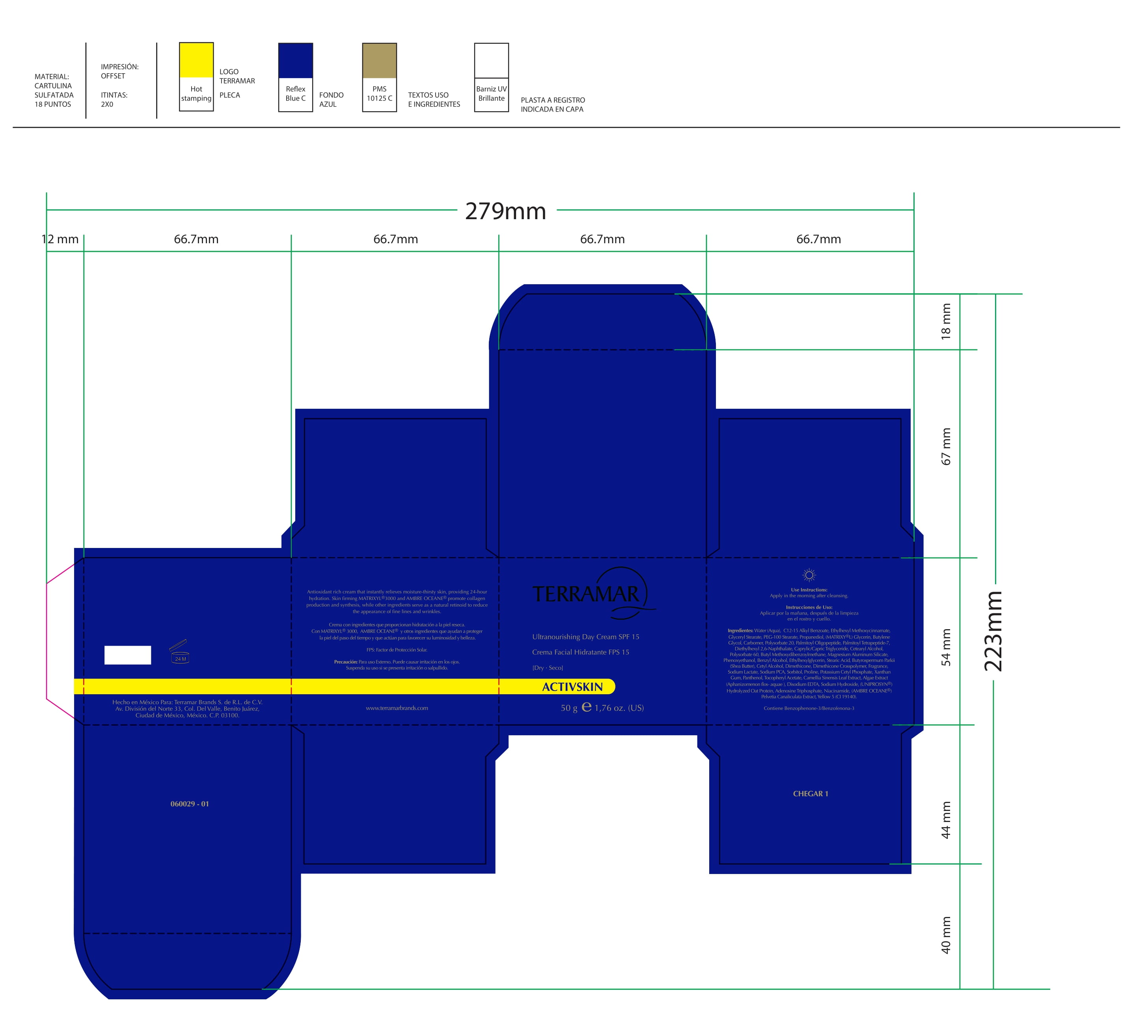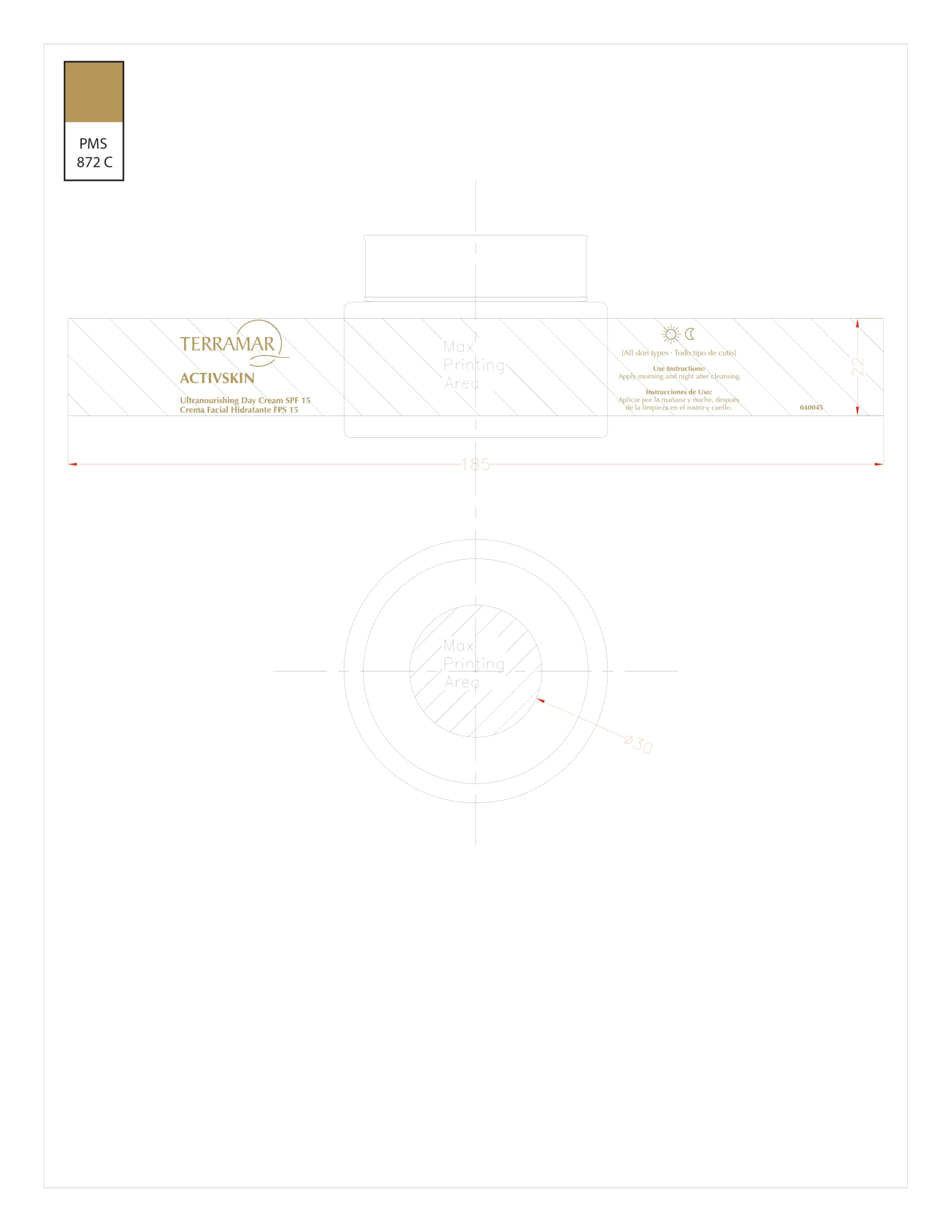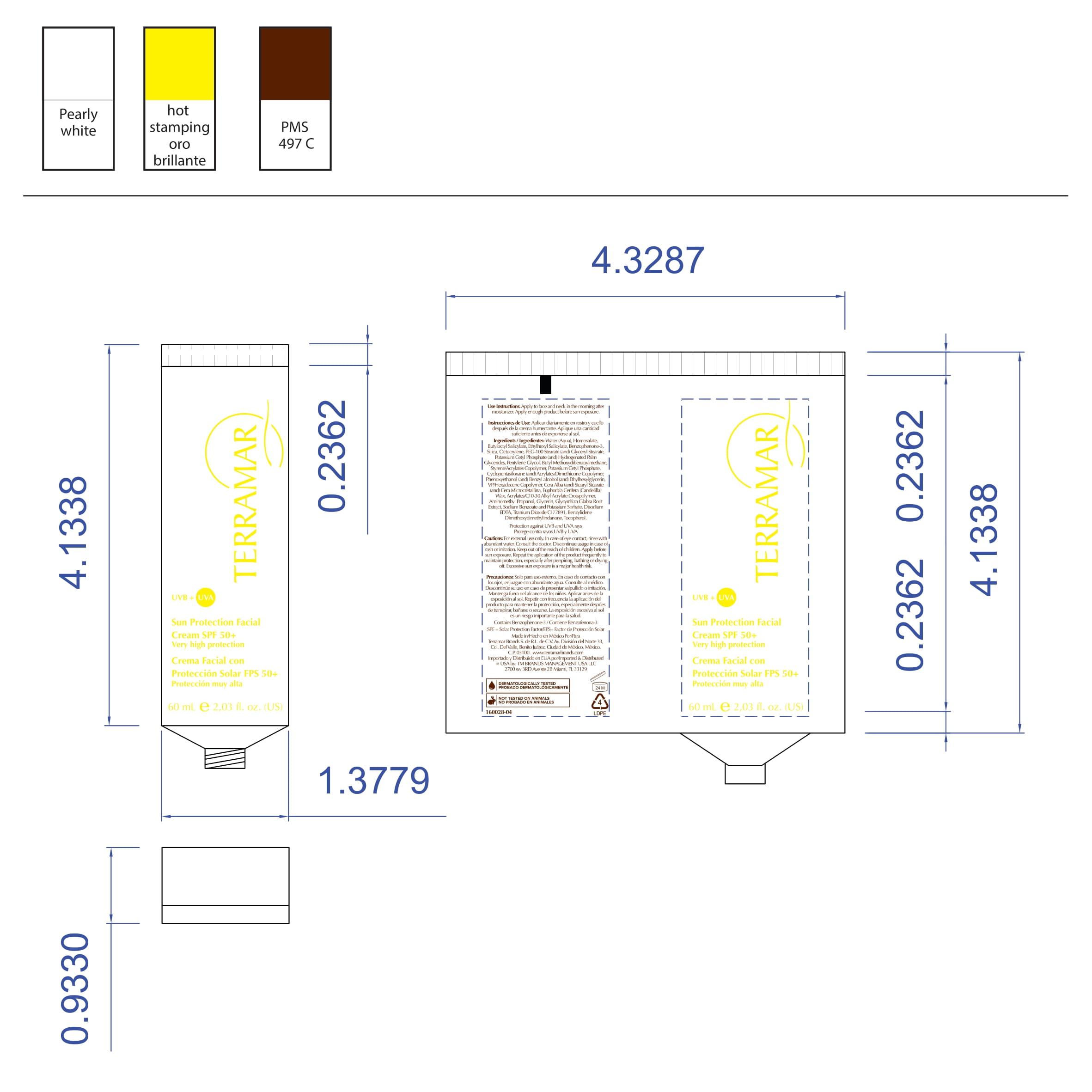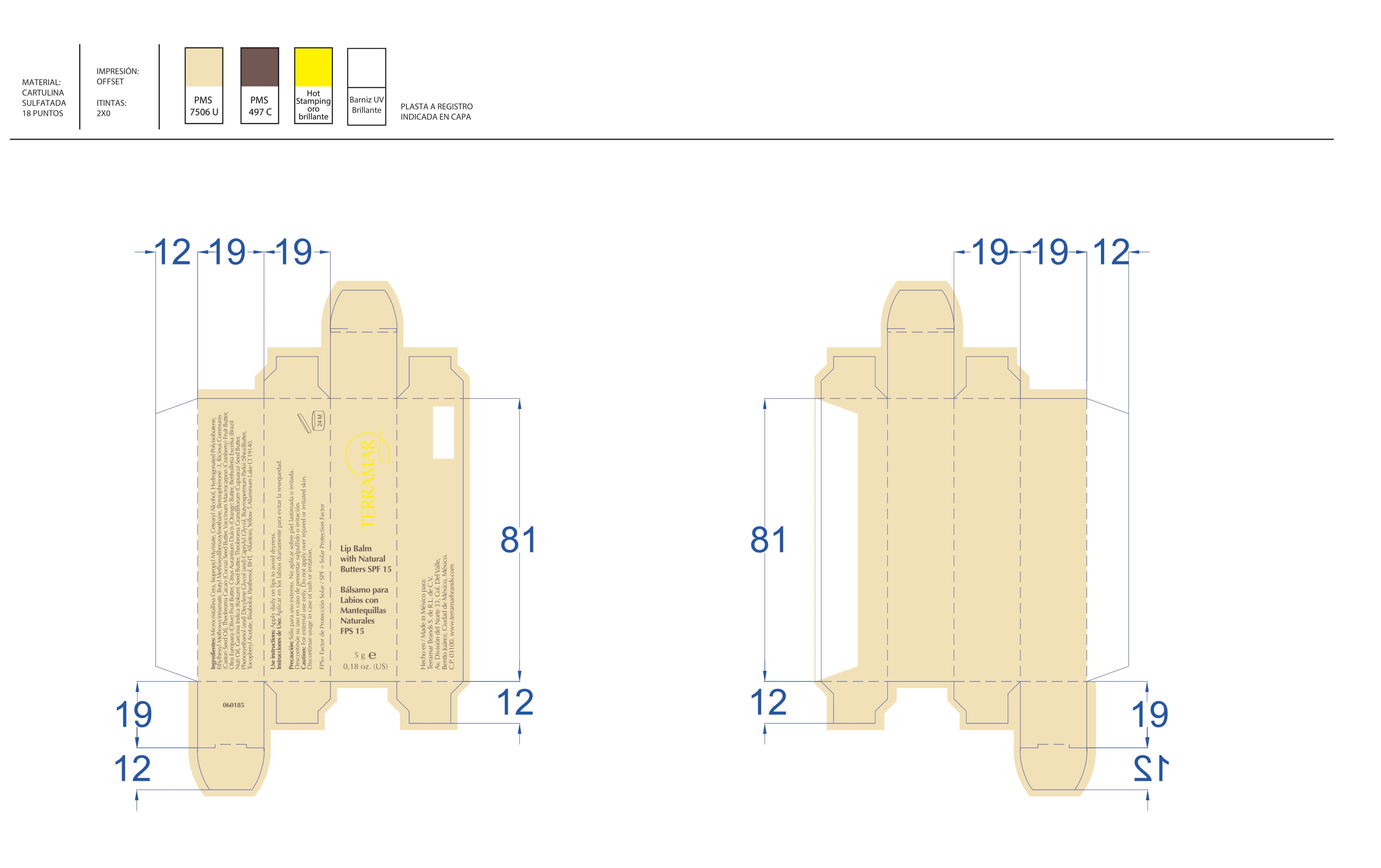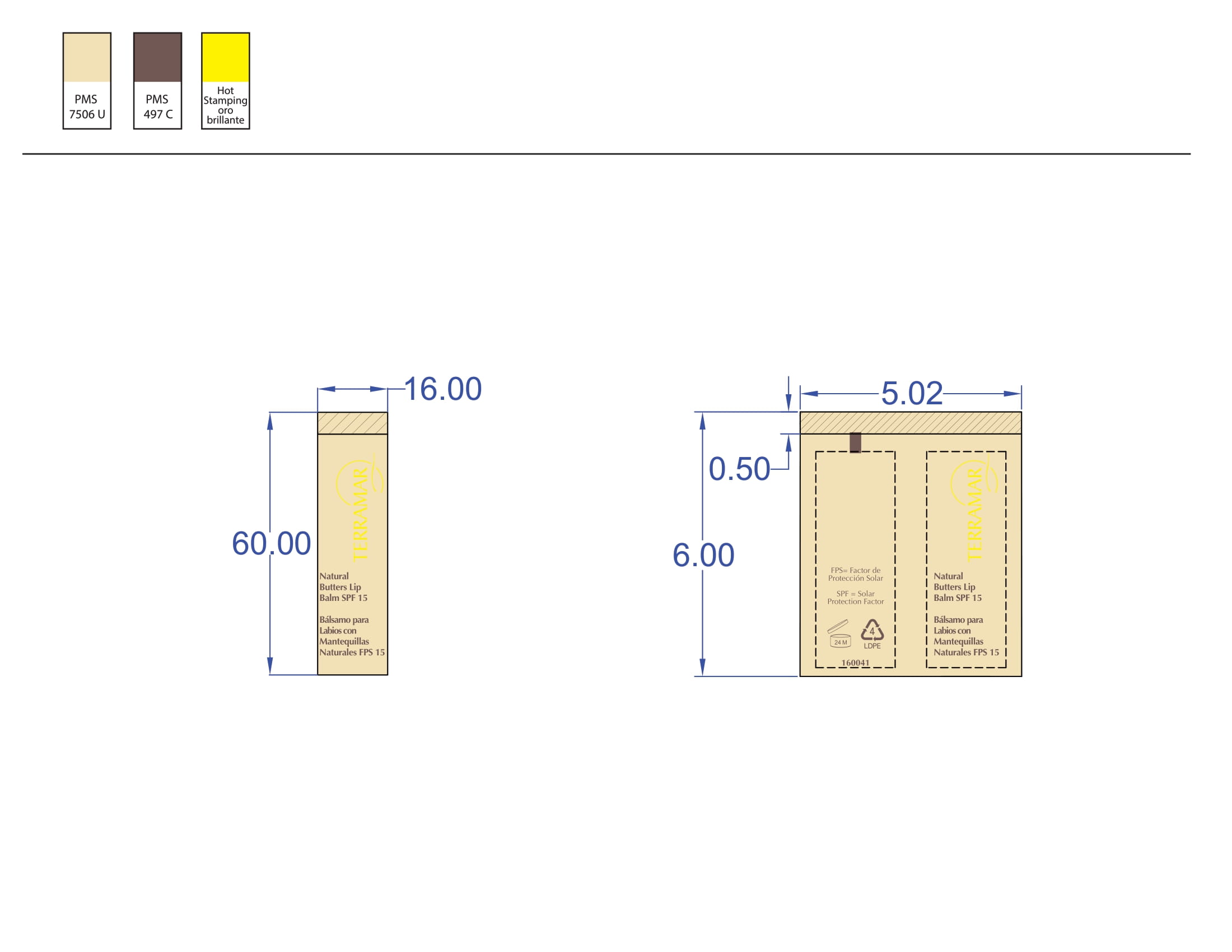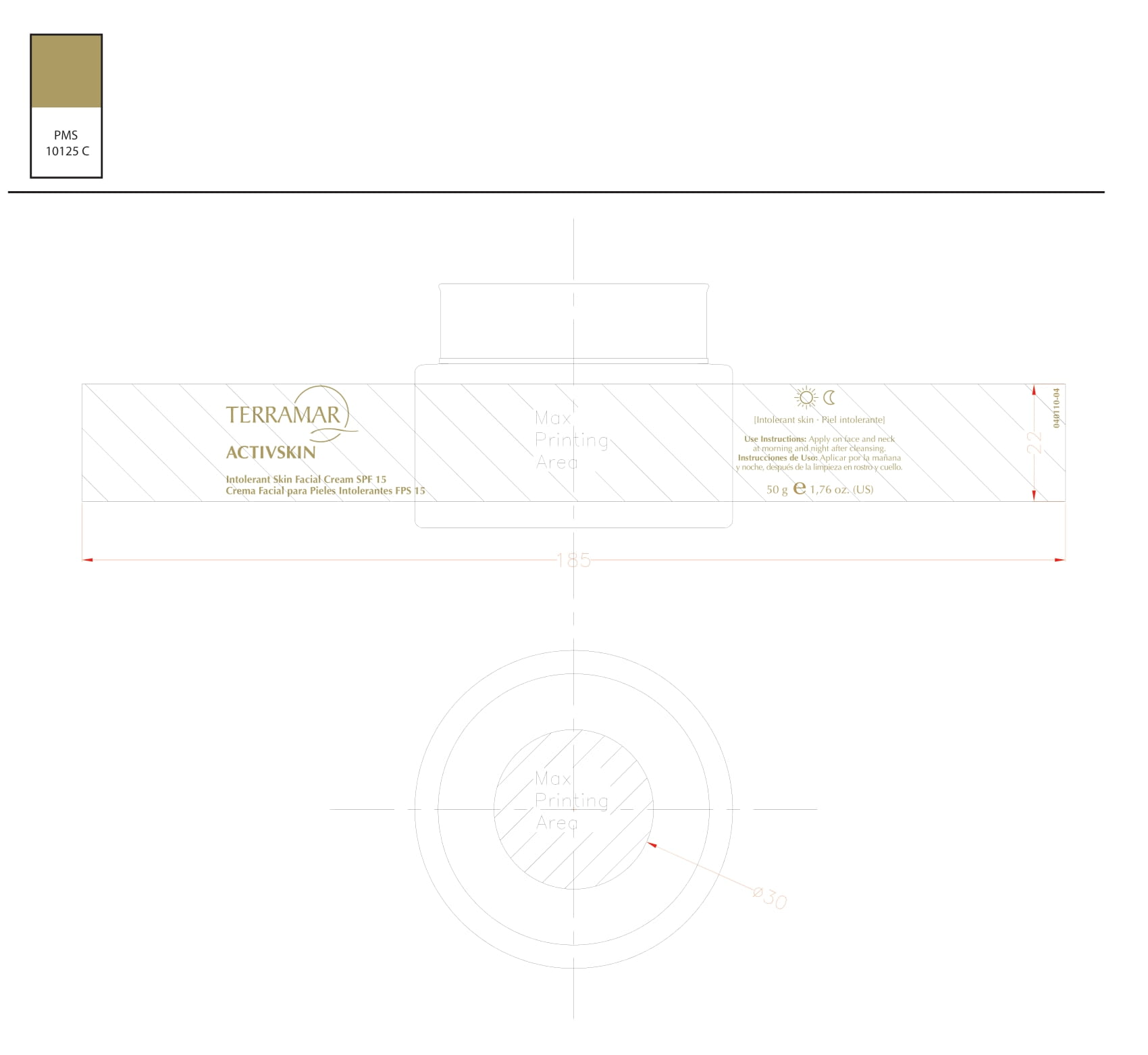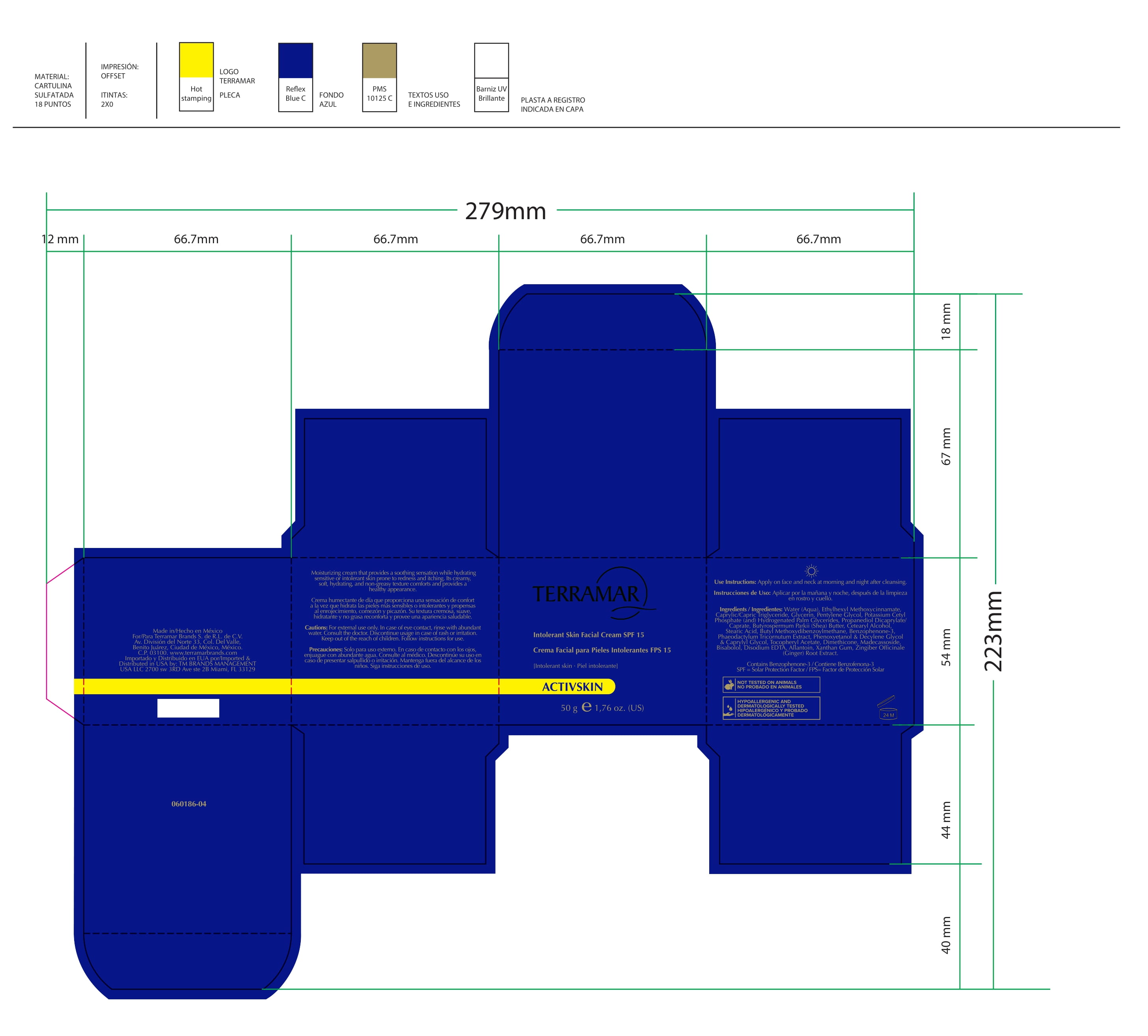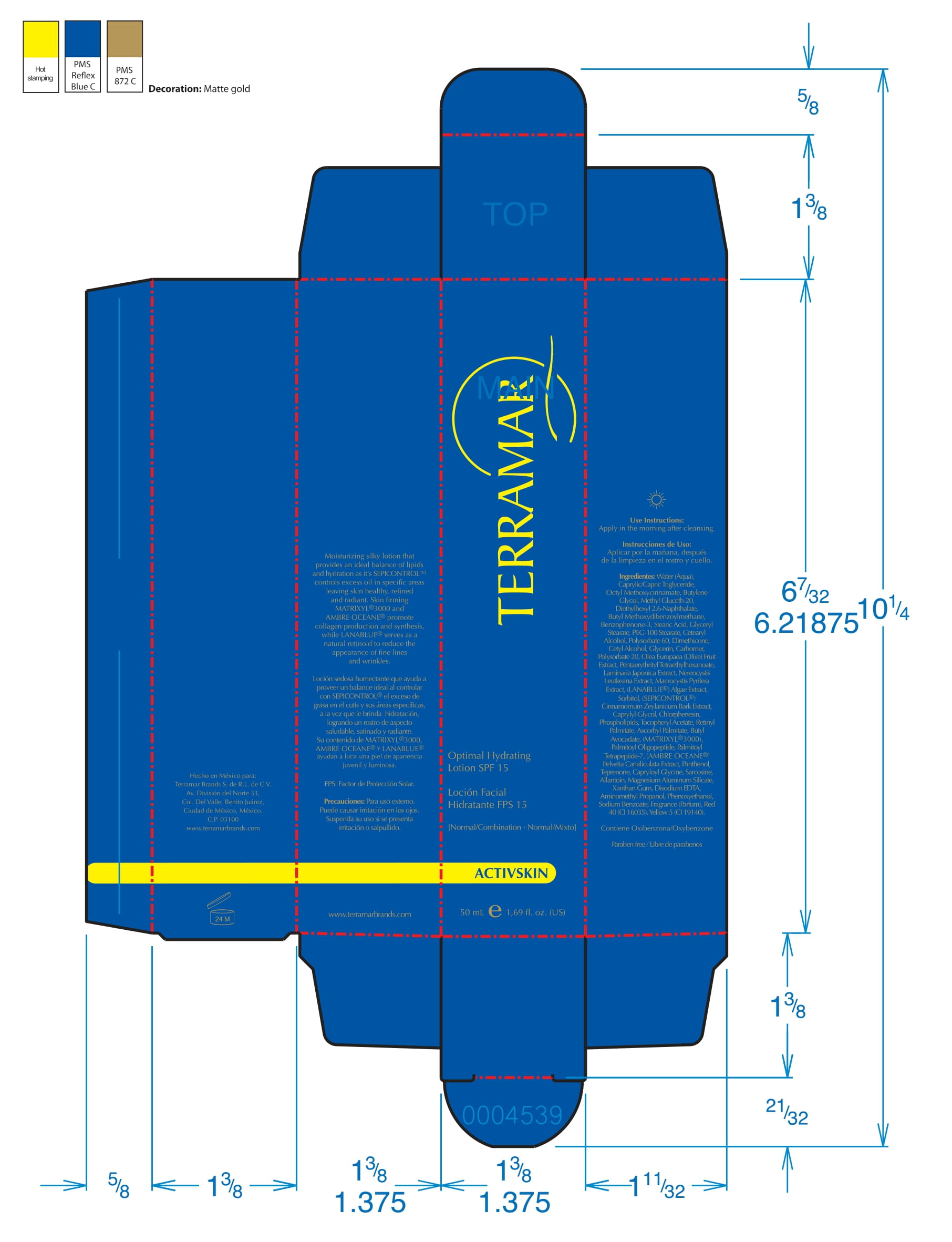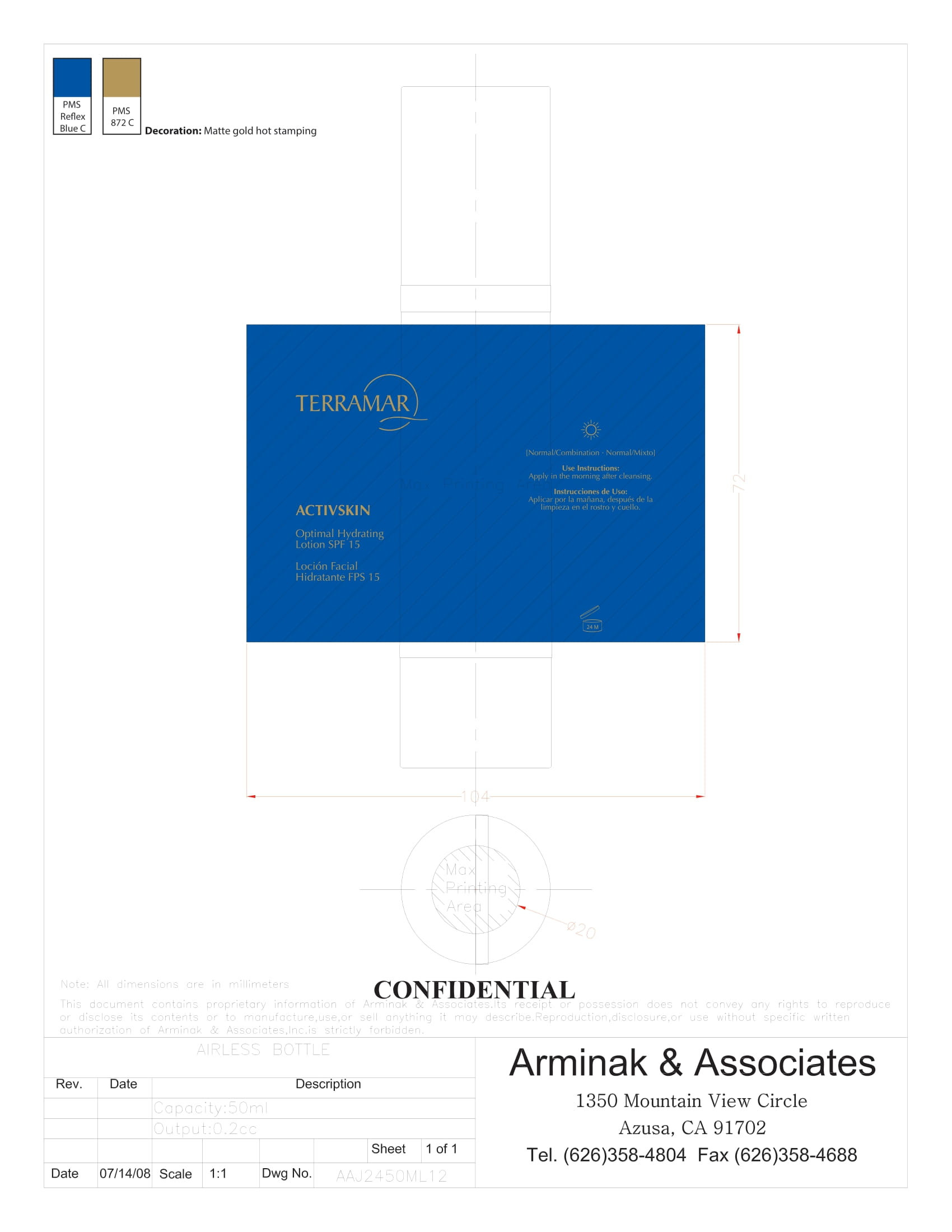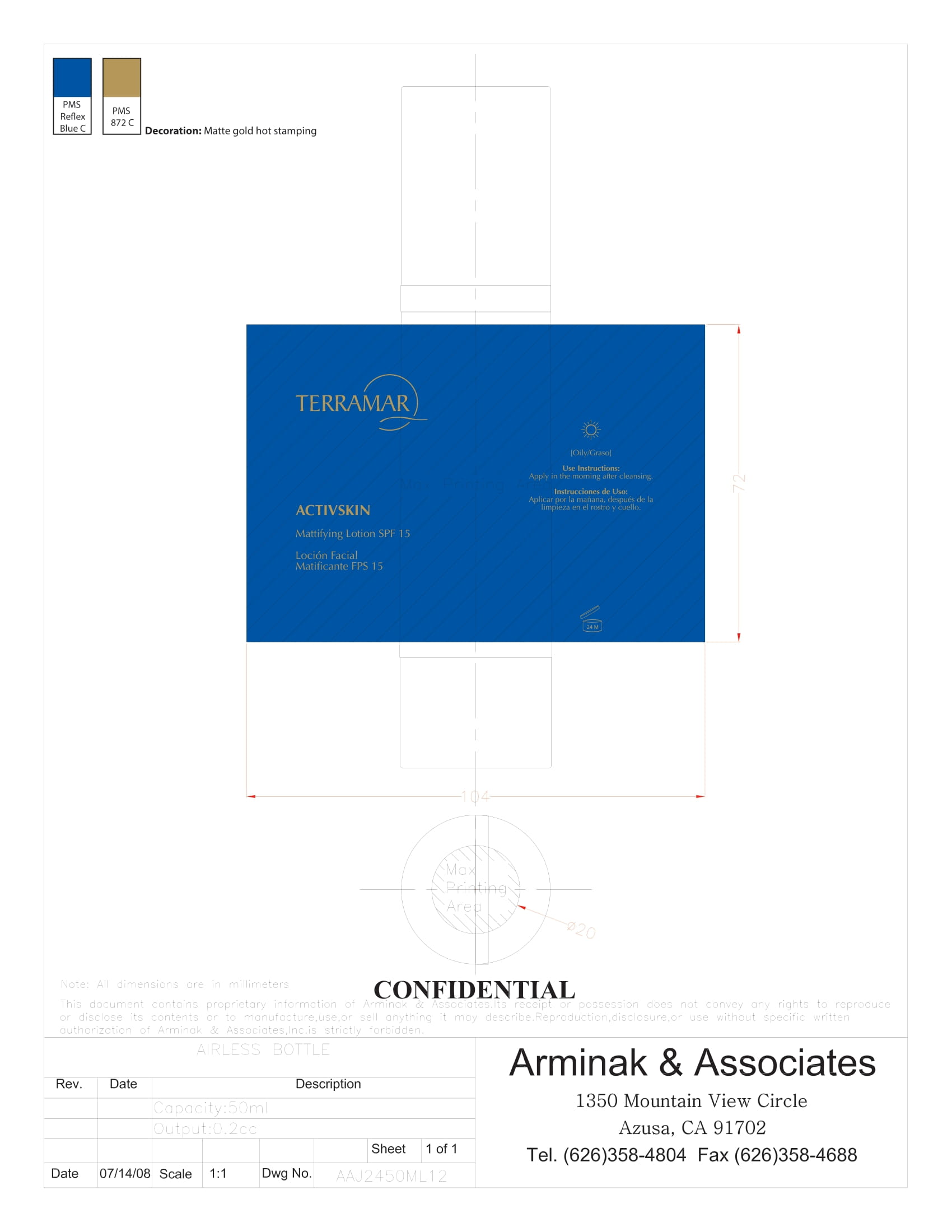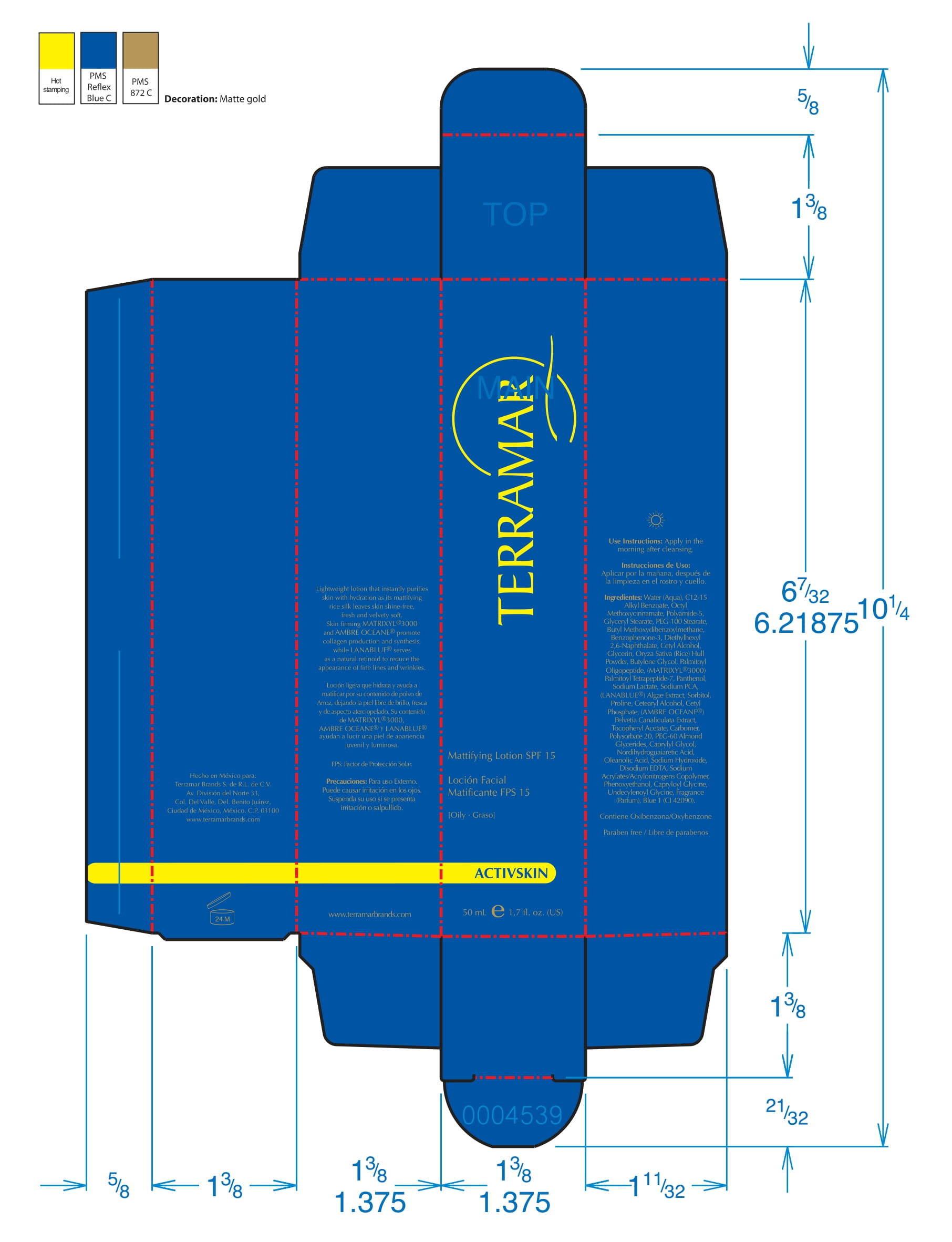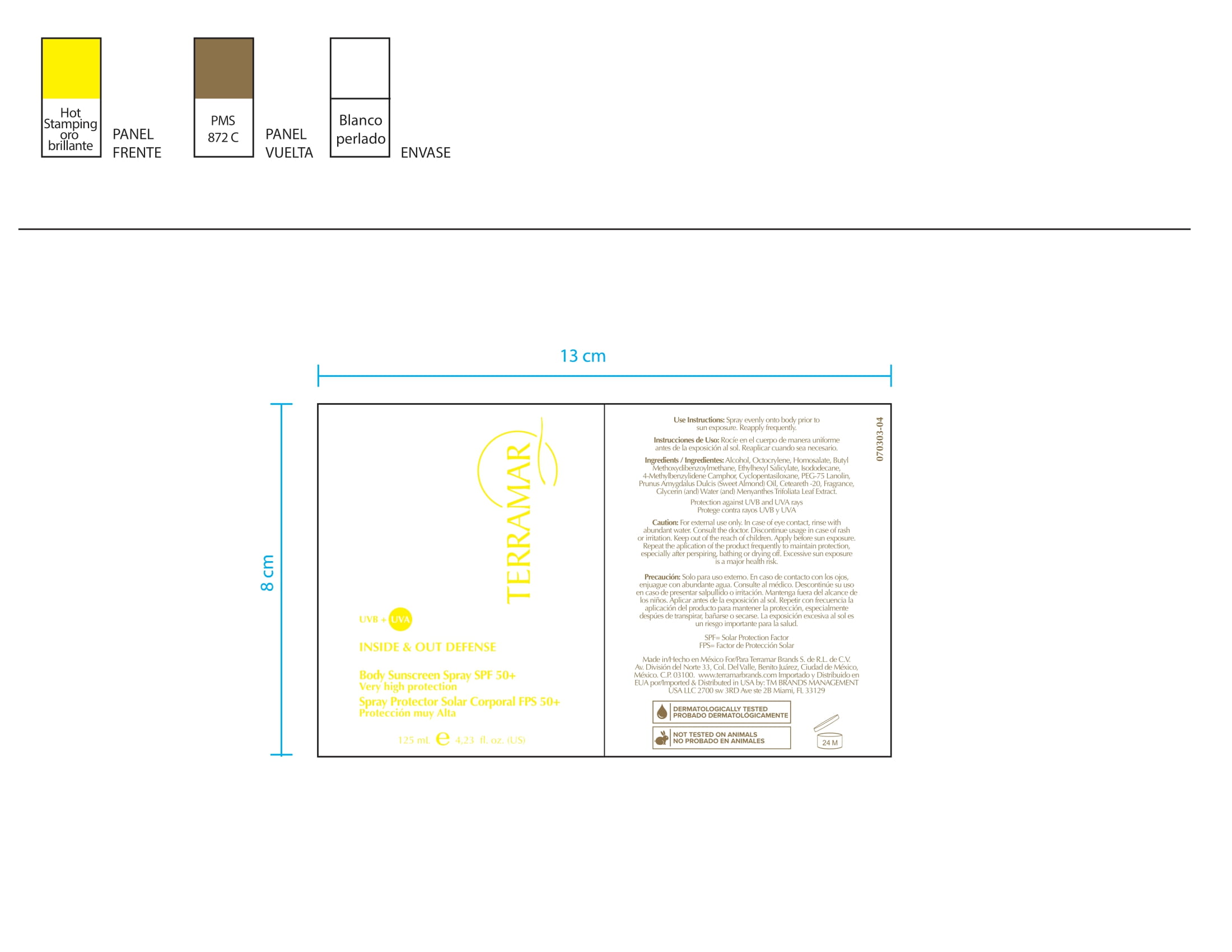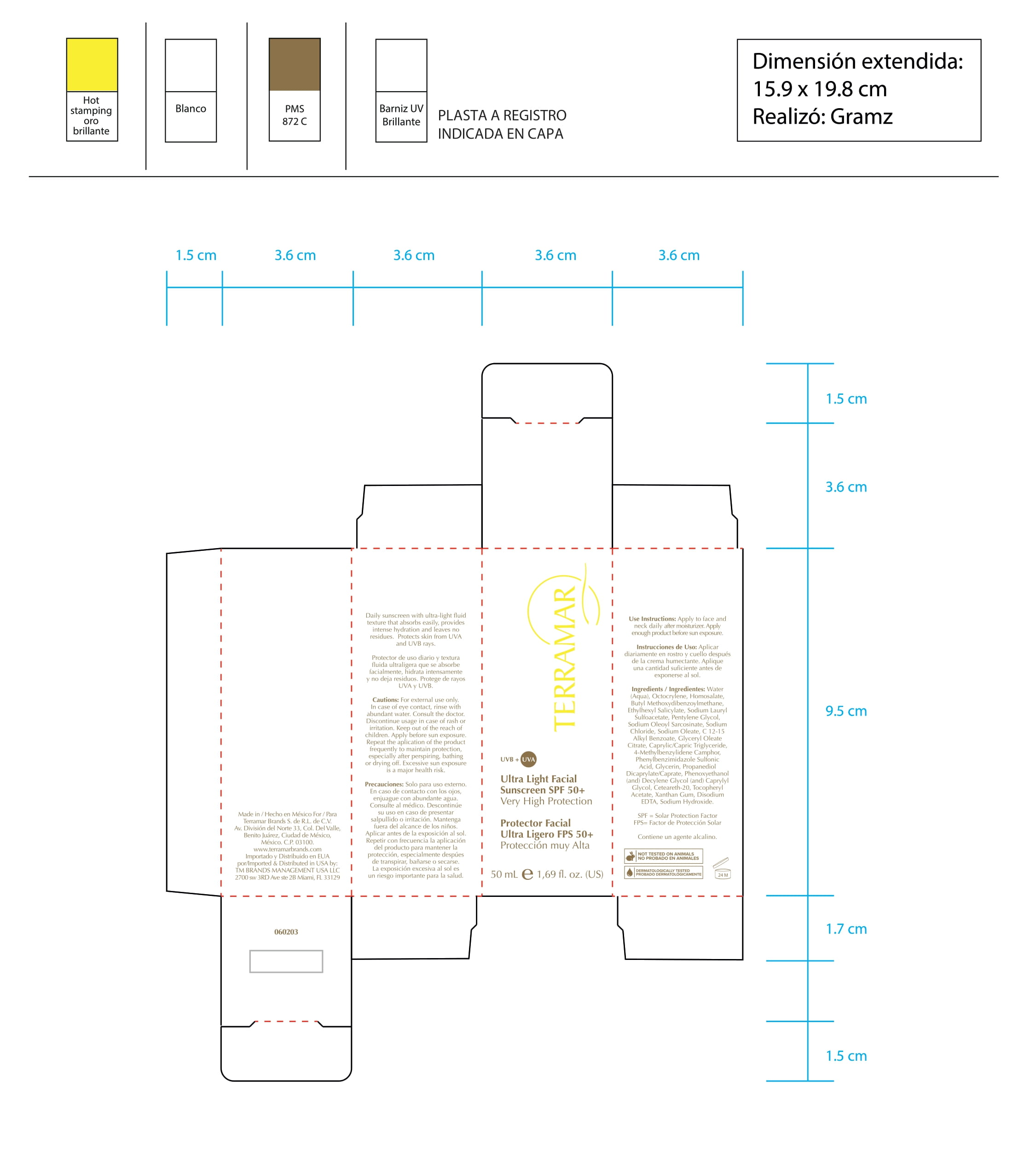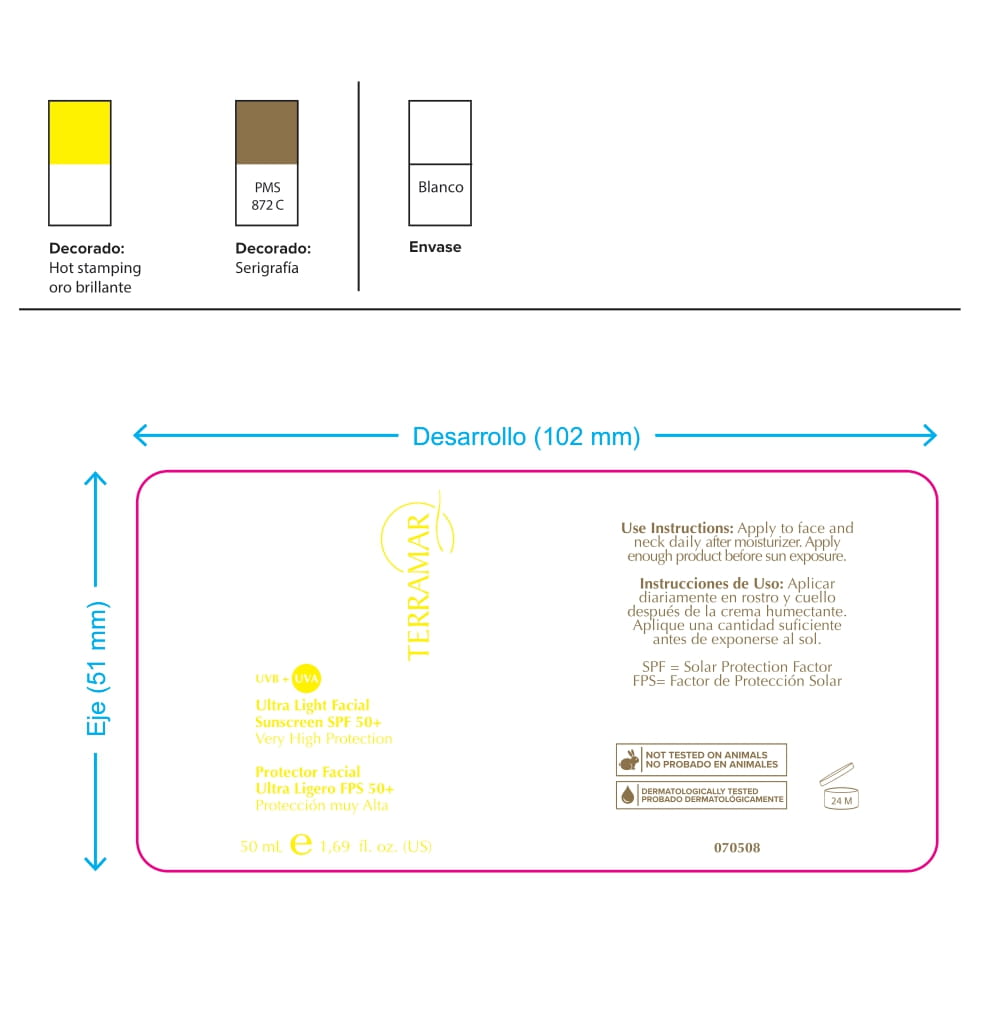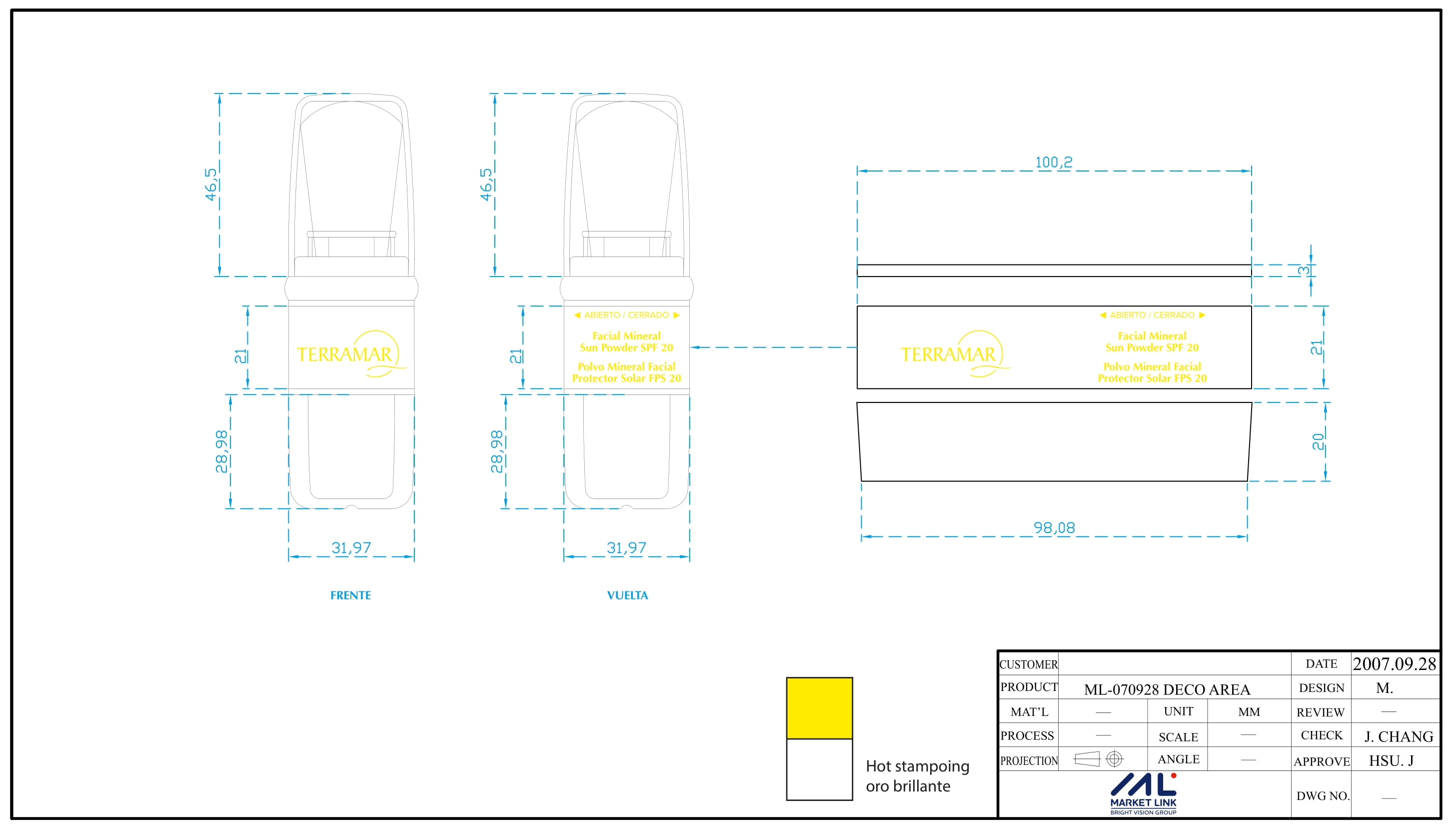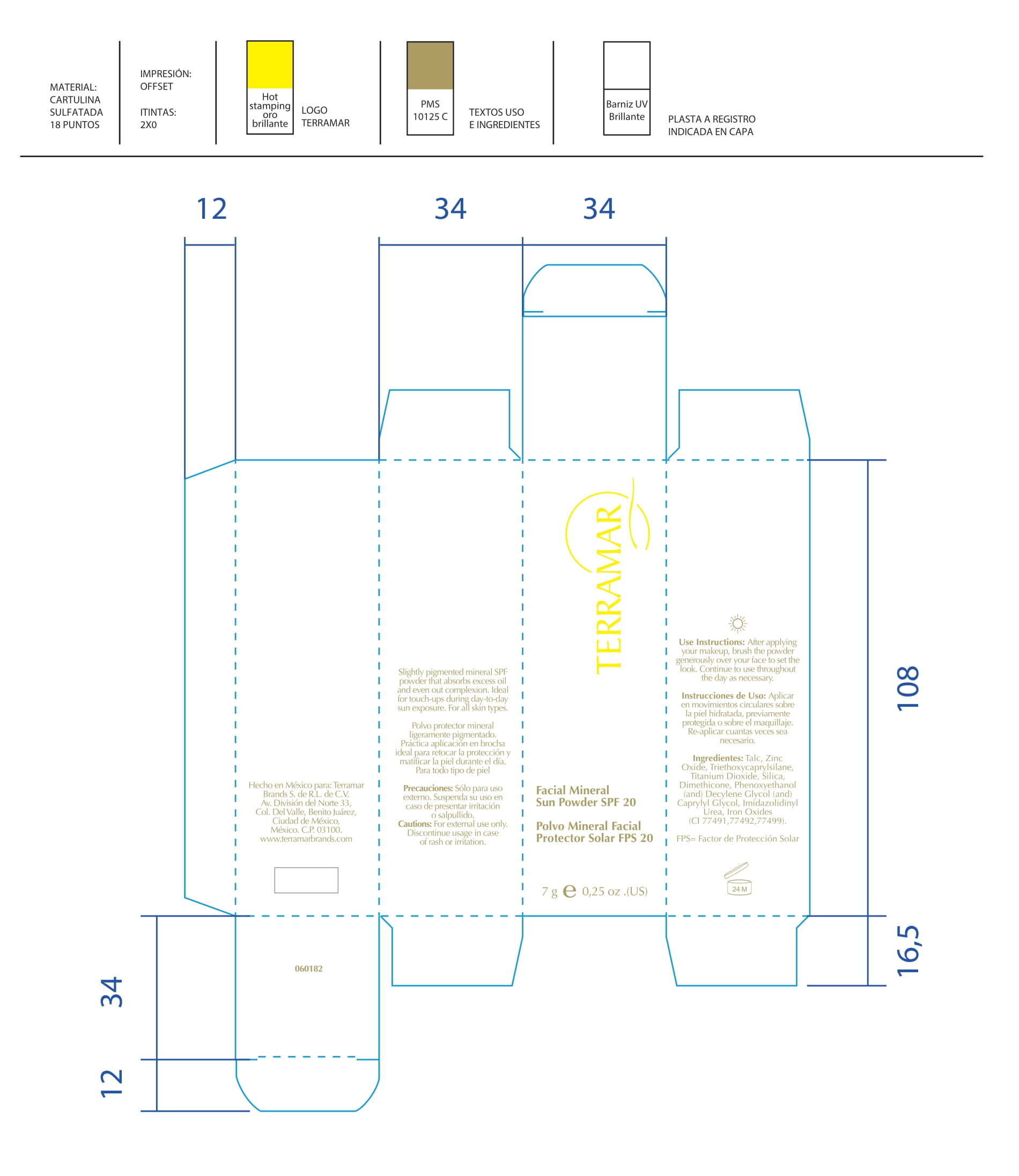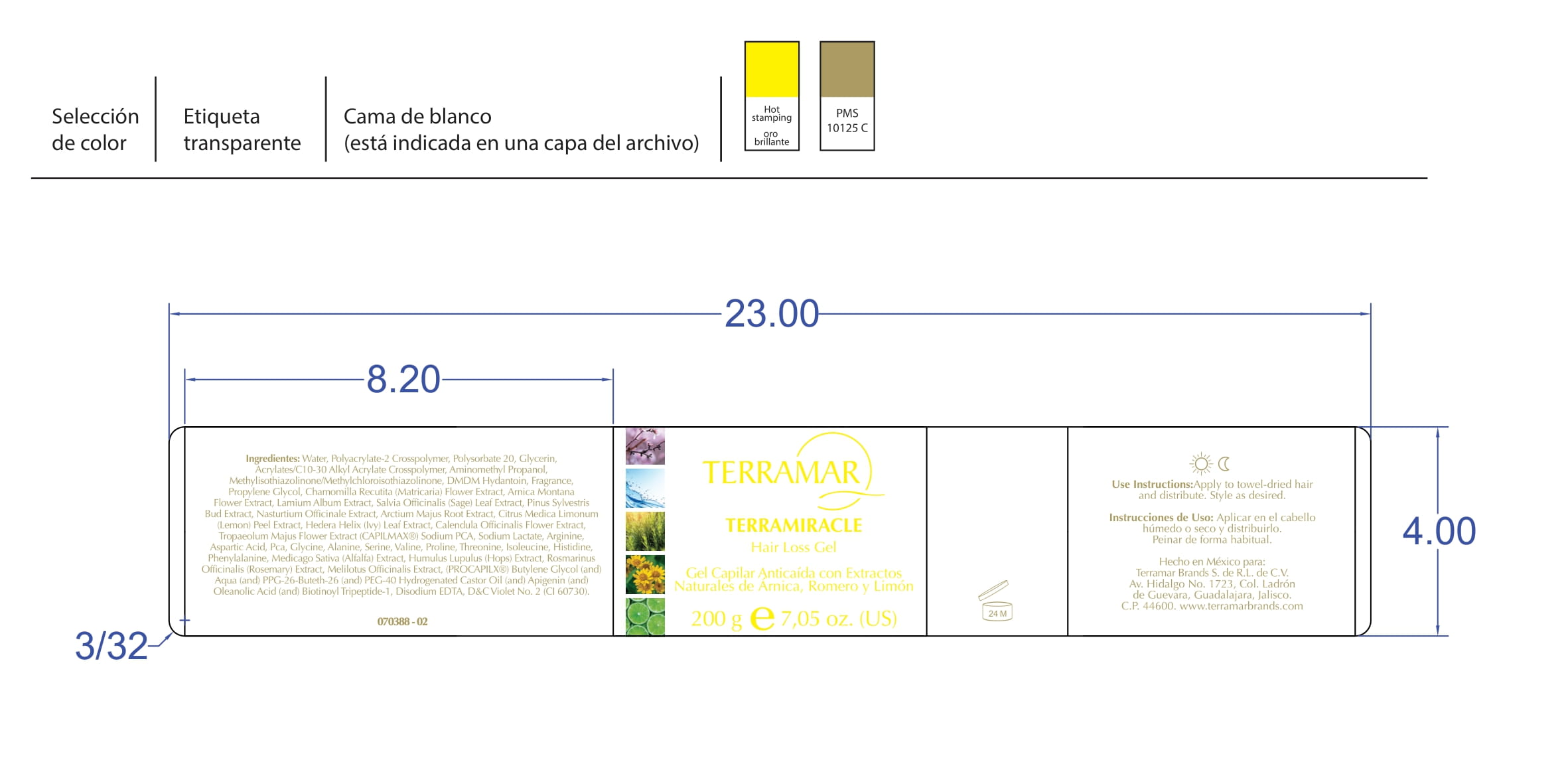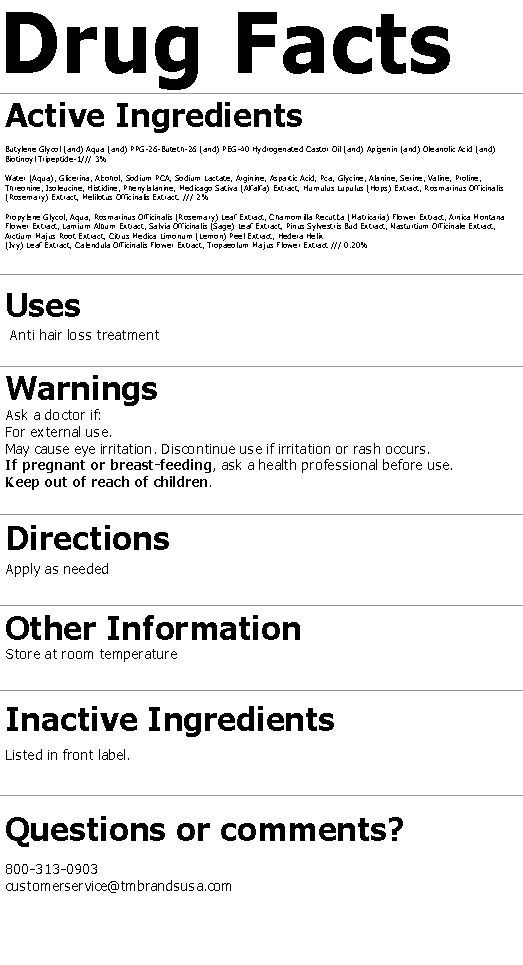 DRUG LABEL: Hydrating Facial Cream SPF 15 Dry Skin
NDC: 82736-008 | Form: CREAM
Manufacturer: TERRAMAR BRANDS S de RL de CV
Category: otc | Type: HUMAN OTC DRUG LABEL
Date: 20220525

ACTIVE INGREDIENTS: OCTINOXATE 0.1 g/1 g
INACTIVE INGREDIENTS: HYDRATED SILICA 0.7 g/1 g; DIMETHICONE 0.1 g/1 g; TITANIUM DIOXIDE 0.1 g/1 g

TERRAMAR BRANDS - SUNSCREEN PRODUCTS

51945-4

51945-

51945-4

51945-

51945-4

51945-4

51945-4

51945-4

51945-4

DRUG FACTS

ACTIVE INGREDIENTS

ask a doctor if:

symptoms

do not use if

keep out of reach of children

PREGNANCY OR BREAST FEEDING

If pregnant or breast-feeding, ask a health professional before use.

Purpose

QUESTIONS

800-313-0903
customerservice@tmbrandsusa.com

Stop use if

When using

Inactive

PACKAGE LABEL

51945-4